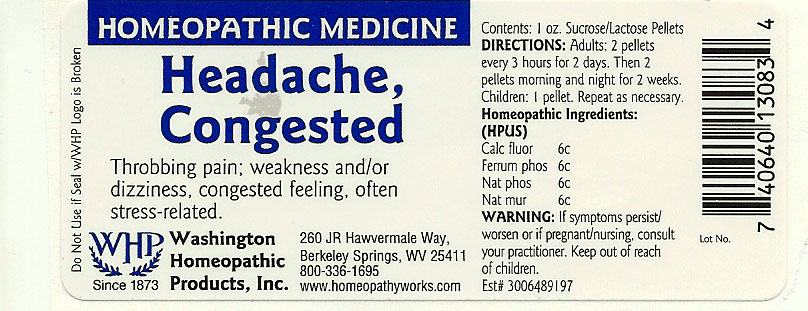 DRUG LABEL: Headache Congested
NDC: 68428-012 | Form: PELLET
Manufacturer: Washington Homeopathic Products
Category: homeopathic | Type: HUMAN OTC DRUG LABEL
Date: 20191223

ACTIVE INGREDIENTS: CALCIUM FLUORIDE 6 [hp_C]/28 g; FERROSOFERRIC PHOSPHATE 6 [hp_C]/28 g; SODIUM PHOSPHATE, DIBASIC, HEPTAHYDRATE 6 [hp_C]/28 g; SODIUM CHLORIDE 6 [hp_C]/28 g
INACTIVE INGREDIENTS: SUCROSE; LACTOSE

DRUG FACTS

ACTIVE INGREDIENTS

CALC FLUOR 6C

FERRUM PHOS 6C

NAT PHOS 6C

NAT MUR 6C

USES

To relieve the symptoms of throbbing pain; weakness and/or dizziness, congested feeling, often stress-related.

KEEP OUT OF REACH OF CHILDREN

Keep this and all medicines out of reach of children.

INDICATIONS

CALC FLUOR Joint pain

FERRUM PHOS Low fever

NAT PHOS Sour belching

NAT MUR Sneezing

STOP USE AND ASK DOCTOR

If symptoms persist/worsen or if pregnant/nursing, stop use and consult your practitioner.

DIRECTIONS

Adults 2 pellets every 3 hours for 2 days. Then 2 pellets morning and night for 2 weeks.

Children: 1 pellet. Repeat as necessary.

INACTIVE INGREDIENTS

Sucrose/Lactose

PRINCIPAL DISPLAY PANEL

Enter section text here